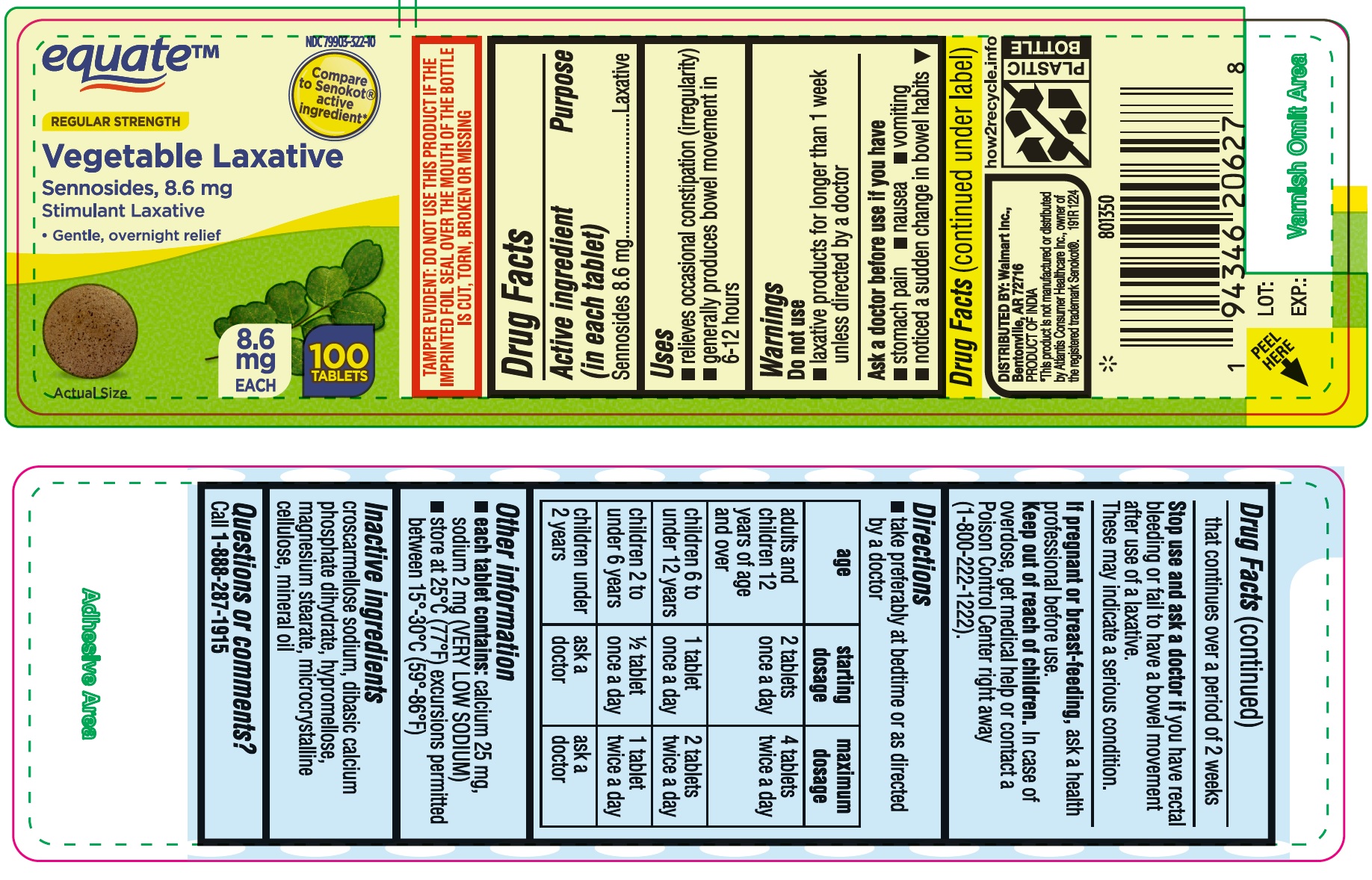 DRUG LABEL: Vegetable Laxative
NDC: 79903-322 | Form: TABLET
Manufacturer: Walmart Inc.
Category: otc | Type: HUMAN OTC DRUG LABEL
Date: 20250414

ACTIVE INGREDIENTS: SENNOSIDES A AND B 8.6 mg/1 1
INACTIVE INGREDIENTS: CROSCARMELLOSE SODIUM; MAGNESIUM STEARATE; CELLULOSE, MICROCRYSTALLINE; DIBASIC CALCIUM PHOSPHATE DIHYDRATE; HYPROMELLOSE, UNSPECIFIED; MINERAL OIL

Walmart Sennosides 8.6 mg Tablets

Active ingredient (in each tablet)

Sennosides 8.6 mg

Purpose

Laxative

Uses

- relieves occasional constipation (irregularity)
- generally produces bowel movement in 6-12 hours

Warnings

-

Do not use

- laxative products for longer than 1 week unless directed by a doctor

Ask a doctor before use if you have

- stomach pain
- nausea
- vomiting
- noticed a sudden change in bowel habits that continues over a period of 2 weeks

Stop use and ask a doctor if

you have rectal bleeding or fail to have a bowel movement after use of a laxative. These may indicate a serious condition.

If pregnant or breast-feeding,

ask a health professional before use.

Keep out of reach of children.

In case of overdose, get medical help or contact a Poison Control Center right away (1-800-222-1222).

Directions

- take preferably at bedtime or as directed by a doctor

age | starting dosage | maximum dosage
adults and children 12 years of age and over | 2 tablets once a day | 4 tablets twice a day
children 6 to under 12 years | 1 tablet once a day | 2 tablets twice a day
children 2 to under 6 years | ½ tablet once a day | 1 tablet twice a day

children under 2 years: starting dosage:ask a doctor, maximum dosage: ask a doctor

Other information

- each tablet contains: calcium 25 mg, sodium 2 mg (VERY LOW SODIUM)
- store at 25°C (77°F) excursions permitted between 15°-30°C (59°-86°F)

Inactive ingredients

croscarmellose sodium, dibasic calcium phosphate dihydrate, hypromellose, magnesium stearate, microcrystalline cellulose, mineral oil

Questions or comments?

Call 1-888-287-1915